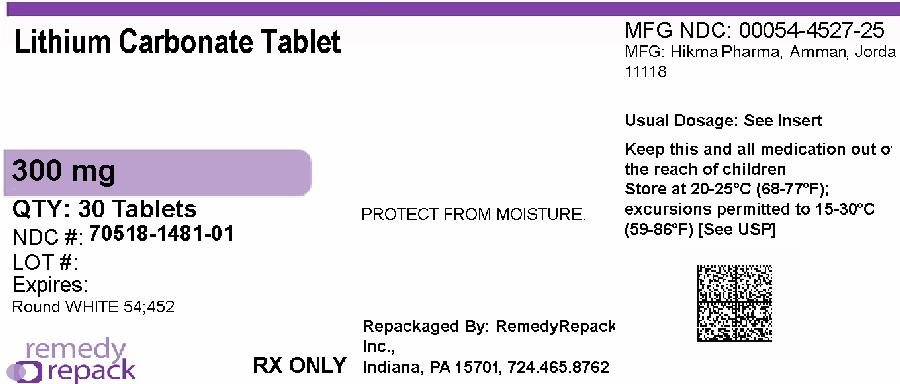 DRUG LABEL: Lithium Carbonate
NDC: 70518-1481 | Form: TABLET
Manufacturer: REMEDYREPACK INC.
Category: prescription | Type: HUMAN PRESCRIPTION DRUG LABEL
Date: 20260123

ACTIVE INGREDIENTS: LITHIUM CARBONATE 300 mg/1 1
INACTIVE INGREDIENTS: CALCIUM STEARATE; MICROCRYSTALLINE CELLULOSE; POVIDONE K30; SODIUM STARCH GLYCOLATE TYPE A POTATO; WATER; SODIUM LAURYL SULFATE

HIGHLIGHTS OF PRESCRIBING INFORMATION

These highlights do not include all the information needed to use LITHIUM and LITHIUM CARBONATE safely and effectively. See full prescribing information for LITHIUM and LITHIUM CARBONATE.
LITHIUM oral solution, for oral use
LITHIUM CARBONATE tablets, for oral use
LITHIUM CARBONATE capsules, for oral use
Initial U.S. Approval: 1970

WARNING: LITHIUM TOXICITY

See full prescribing information for complete boxed warning.

Lithium toxicity is closely related to serum lithium concentrations, and can occur at doses close to therapeutic concentrations. Facilities for prompt and accurate serum lithium determinations should be available before initiating therapy (2.3, 5.1).

1 INDICATIONS AND USAGE

Lithium is a mood-stabilizing agent indicated as monotherapy for the treatment of bipolar I disorder:

- Treatment of acute manic and mixed episodes in patients 7 years and older (1)
- Maintenance treatment in patients 7 years and older (1)

2 DOSAGE AND ADMINISTRATION

- Recommended starting dosage for adults and pediatric patients over 30 kg (2.2):
  - Tablets or Capsules: 300 mg, three times daily, or
  - Oral Solution: 8mEq lithium (5 mL) three times daily
- Recommended starting dosage for pediatric patients 20 to 30 kg (2.2):
  - Tablets or Capsules: 300 mg twice daily, or
  - Oral Solution: 8mEq (5mL), twice daily
- Obtain serum lithium concentration assay after 3 days, drawn 12 hours after the last oral dose and regularly until patient is stabilized.
- Acute Manic or Mixed Episodes (patients 7 years and older): Titrate to serum lithium concentrations 0.8 to 1.2 mEq/L (2.2).
- Maintenance Treatment for Bipolar I Disorder (patients 7 years and older): Titrate to serum lithium concentrations 0.8 to 1 mEq/L (2.2).
- Pre-treatment Screening: Evaluate renal function, vital signs, electrolytes, thyroid function, concurrent medications, and pregnancy status (2.1).
- Mild to Moderate Renal Impairment (CLer 30 to 89 mL/min): Start with dosages less than those for patients with normal renal function, titrate slowly with frequent monitoring (2.5).
- Severe Renal Impairment (CLer<30mL/min): Avoid use of lithium (2.5).

3 DOSAGE FORMS AND STRENGTHS

- Tablets: 300 mg of lithium carbonate (3)

4 CONTRAINDICATIONS

Known hypersensitivity to any inactive ingredient in the drug product. (4)

5 WARNINGS AND PRECAUTIONS

- Lithium-Induced Polyuria: May develop during initiation of treatment. Increases risk of lithium toxicity. Educate patient to avoid dehydration. Monitor for lithium toxicity and metabolic acidosis. Discontinue lithium or treat with amiloride as a therapeutic agent (5.2).
- Hyponatremia: Symptoms are more severe with faster-onset hyponatremia. Dehydration from protracted sweating, diarrhea, or elevated temperatures from infection increases risk of hyponatremia and lithium toxicity. Educate patients on maintaining a normal diet with salt and staying hydrated. Monitor for and treat hyponatremia and lithium toxicity, which may necessitate a temporary reduction or cessation of lithium and infusion of serum sodium (5.3).
- Lithium-Induced Chronic Kidney Disease: Associated with structural changes in patients on chronic lithium therapy. Monitor kidney function during treatment with lithium (5.4).
- Encephalopathic Syndrome: Increased risk in patients treated with lithium and an antipsychotic. Monitor routinely for changes to cognitive function (5.5).
- Hypothyroidism and Hyperthyroidism: Monitor thyroid function regularly (5.7).
- Hypercalcemia and Hyperparathyroidism: Associated with long-term lithium use. Monitor serum calcium (5.8).

6 ADVERSE REACTIONS

Common Adverse Reactions:

- Adult Patients: fine hand tremor, polyuria, mild thirst, nausea, general discomfort during initial treatment (6)
- Pediatric Patients (7-17 years): nausea/vomiting, polyuria, thyroid abnormalities, tremor, thirst/polydipsia, dizziness, rash/dermatitis, ataxia/gait disturbance, decreased appetite, and blurry vision (6)

To report SUSPECTED ADVERSE REACTIONS, contact West-Ward Pharmaceuticals Corp. at 1-800-962-8364 or FDA at 1-800-FDA-1088 or www.fda.gov/medwatch.

7 DRUG INTERACTIONS

- Diuretics, NSAID, renin-angiotensin system antagonists, or metronidazole may increase lithium serum concentrations. Recommend frequent monitoring of serum lithium concentration and adjust dosage when necessary. (2.3, 7.1)
- Serotonergic Agents: Increased risk of serotonin syndrome when co-administered with lithium. (5.6, 7.1)
- Antipsychotics: There have been reports of neurologic adverse reactions in patients treated with lithium and an antipsychotic, ranging from extrapyramidal symptoms to neuroleptic malignant syndrome. (5.5, 7.1)

8 USE IN SPECIFIC POPULATIONS

- Pregnancy: May cause fetal and/or neonatal harm (8.1)
- Renal Impairment: Use caution during dose selection, starting with dosages less than those for patients with normal renal function while carefully monitoring for side effects (2.5, 6)

FULL PRESCRIBING INFORMATION

WARNING: LITHIUM TOXICITY

Lithium toxicity is closely related to serum lithium concentrations, and can occur at doses close to therapeutic concentrations. Facilities for prompt and accurate serum lithium determinations should be available before initiating treatment [see Dosage and Administration (2.3), Warnings and Precautions (5.1)] .

1 INDICATIONS AND USAGE

Lithium is a mood-stabilizing agent indicated as monotherapy for the treatment of bipolar I disorder:

- Treatment of acute manic and mixed episodes in patients 7 years and older [see Clinical Studies (14)]
- Maintenance treatment in patients 7 years and older [see Clinical Studies (14)]

2 DOSAGE AND ADMINISTRATION

2.1 Pre-treatment Screening

Before initiating treatment with lithium, renal function, vital signs, serum electrolytes, and thyroid function should be evaluated. Concurrent medications should be assessed, and if the patient is a woman of childbearing potential, pregnancy status and potential should be considered.

2.2 Recommended Dosage

See Table 1 for dosage recommendations for acute and maintenance treatment of bipolar I disorder in adult and pediatric patients (7 to 17 years).

Obtain serum lithium concentration assay after 3 days, drawn 12 hours after the last oral dose and regularly until patient is stabilized. Fine hand tremor, polyuria, and thirst may occur during initial therapy for the acute manic phase and may persist throughout treatment. Nausea and general discomfort may also appear during the first few days of lithium administration. These adverse reactions may subside with continued treatment, concomitant administration with food, or temporary reduction or cessation of dosage.

Table 1. Lithium Dosing for Bipolar I Disorder
Patient Group | Formulation | Starting Dose | 1. Dose Titration | Acute Goal |  | Maintenance Goal
Patient Group | Formulation | Starting Dose | 1. Dose Titration | Serum Level | Usual Dose | Serum Level | Usual Dose
Adult and Pediatric Patients over 30 kg | Tablets or capsules | 300 mg three times daily | 1. 300 mg every 3 days | 0.8 to 1.2 mEq/L | 600 mg two to three times daily | 0.8 to 1.0 mEq/L | 300 to 600 mg two to three times daily
Adult and Pediatric Patients over 30 kg | Liquid | 8 mEq (5 mL) three times daily | 1. 8 mEq (5 mL) every 3 days | 0.8 to 1.2 mEq/L | 16 mEq (10mL) two to three times daily | 0.8 to 1.0 mEq/L | 8 to 16 mEq (5 to 10 mL) two to three times daily
Pediatric Patients 20 to 30 kg | Tablets or capsules | 300 mg twice daily | 1. 300 mg weekly | 0.8 to 1.2 mEq/L | 600 to 1500 mg in divided doses daily | 0.8 to 1.0 mEq/L | 600 to 1200 mg in divided doses daily
Pediatric Patients 20 to 30 kg | Liquid | 8 mEq (5 mL) twice daily | 1. 8 mEq (5 mL) weekly | 0.8 to 1.2 mEq/L | 16 to 40 mEq (10 to 25 mL) in divided doses daily | 0.8 to 1.0 mEq/L | 16 to 32 mEq (10 to 20 mL) in divided doses daily

Each 5 mL of Lithium Oral Solution contains 8 mEq of lithium ion (Li+) which is equivalent to the amount of lithium in 300 mg of lithium carbonate. See Table 2 for lithium carbonate and lithium oral solution dose conversion.

Table 2. Lithium Carbonate and Lithium Oral Solution Dose Conversion

Lithium Carbonate Tablets or Capsules | Lithium Oral Solution
150 mg | 4 mEq (2.5 mL)
300 mg | 8 mEq (5 mL)
600 mg | 16 mEq (10 mL)

2.3 Serum Lithium Monitoring

Blood samples for serum lithium determination should be drawn immediately prior to the next dose when lithium concentrations are relatively stable (i.e., 12 hours after the previous dose). Total reliance must not be placed on serum concentrations alone. Accurate patient evaluation requires both clinical and laboratory analysis.

In addition to regular monitoring of serum lithium concentrations for patients on maintenance treatment, serum lithium concentrations should be monitored after any change in dosage, concurrent medication (e.g., diuretics, non-steroidal anti-inflammatory drugs, renin-angiotensin system antagonists, or metronidazole), marked increase or decrease in routinely performed strenuous physical activity (such as an exercise program) and in the event of a concomitant disease [see Boxed Warning, Warnings and Precautions (5.1), Drug Interactions (7.1)] .

Patients abnormally sensitive to lithium may exhibit toxic signs at serum concentrations that are within what is considered the therapeutic range. Geriatric patients often respond to reduced dosage, and may exhibit signs of toxicity at serum concentrations ordinarily tolerated by other patients [see Specific Populations (8.5)] .

2.4 Dosage Adjustments during Pregnancy and the Postpartum Period

If the decision is made to continue lithium treatment during pregnancy, monitor serum lithium concentrations and adjust the dosage as needed in a pregnant woman because renal lithium clearance increases during pregnancy. Avoid sodium restriction or diuretic administration. To decrease the risk of postpartum lithium intoxication, decrease or discontinue lithium therapy two to three days before the expected delivery date to reduce neonatal concentrations and reduce the risk of maternal lithium intoxication due to the change in vascular volume which occurs during delivery. At delivery, vascular volume rapidly decreases and the renal clearance of lithium may decrease to pre-pregnancy concentrations. Restart treatment at the preconception dose when the patient is medically stable after delivery with careful monitoring of serum lithium concentrations [see Warnings and Precautions (5.1) and Use in Specific Populations (8.1)] .

2.5 Dosage Adjustments for Patients with Renal Impairment

Start patients with mild to moderately impaired renal function (creatinine clearance 30 to 89 mL/min evaluated by Cockcroft-Gault) with dosages less than those for patients with normal renal function [see Dosage and Administration (2.2)] . Titrate slowly while frequently monitoring serum lithium concentrations and monitoring for signs of lithium toxicity. Lithium is not recommended for use in patients with severe renal impairment (creatinine clearance less than 30 mL/min evaluated by Cockcroft-Gault) [see Use in Specific Populations (8.6)] .

3 DOSAGE FORMS AND STRENGTHS

Each 300 mg tablet for oral administration contains: lithium carbonate USP and is a white to off-white, biconvex tablet, scored on one side with product identification "54 452" debossed on the other side.

4 CONTRAINDICATIONS

Lithium is contraindicated in patients with known hypersensitivity to any inactive ingredient in the lithium carbonate tablet or capsule or lithium citrate products [see Adverse Reactions (6)].

5 WARNINGS AND PRECAUTIONS

5.1 Lithium Toxicity

The toxic concentrations for lithium (≥1.5 mEq/L) are close to the therapeutic range (0.8 to 1.2mEq/L). Some patients abnormally sensitive to lithium may exhibit toxic signs at serum concentrations that are considered within the therapeutic range [see Boxed Warning, Dosage and Administration (2.3)] . Lithium may take up to 24 hours to distribute into brain tissue, so occurrence of acute toxicity symptoms may be delayed.

Neurological signs of lithium toxicity range from mild neurological adverse reactions such as fine tremor, lightheadedness, lack of coordination, and weakness; to moderate manifestations like giddiness, apathy, drowsiness, hyperreflexia, muscle twitching, ataxia, blurred vision, tinnitus, and slurred speech; and severe manifestations such as clonus, confusion, seizure, coma, and death. In rare cases, neurological sequelae may persist despite discontinuing lithium treatment and may be associated with cerebellar atrophy. Cardiac manifestations involve electrocardiographic changes, such as prolonged QT interval, ST and T-wave changes and myocarditis. Renal manifestations include urine concentrating defect, nephrogenic diabetes insipidus, and renal failure. Respiratory manifestations include dyspnea, aspiration pneumonia, and respiratory failure. Gastrointestinal manifestations include nausea, vomiting, diarrhea, and bloating. No specific antidote for lithium poisoning is known [see Overdosage (10)] .

The risk of lithium toxicity is increased by:

- Recent onset of concurrent febrile illness
- Concomitant administration of drugs which increase lithium serum concentrations by pharmacokinetic interactions or drugs affecting kidney function [ see Drug Interactions (7)].
- Acute ingestion
- Impaired renal function
- Volume depletion or dehydration
- Significant cardiovascular disease
- Changes in electrolyte concentrations (especially sodium and potassium)

Monitor for signs and symptoms of lithium toxicity. If symptoms occur, decrease dosage or discontinue lithium treatment.

5.2 Lithium-Induced Polyuria

Chronic lithium treatment may be associated with diminution of renal concentrating ability, occasionally presenting as nephrogenic diabetes insipidus, with polyuria and polydipsia. The concentrating defect and natriuretic effect characteristic of this condition may develop within weeks of lithium initiation. Lithium can also cause renal tubular acidosis, resulting in hyperchloremic metabolic acidosis. Such patients should be carefully managed to avoid dehydration with resulting lithium retention and toxicity. This condition is usually reversible when lithium is discontinued, although for patients treated with long-term lithium, nephrogenic diabetes insipidus may be only partly reversible upon discontinuation of lithium. Amiloride may be considered as a therapeutic agent for lithium-induced nephrogenic diabetes insipidus.

5.3 Hyponatremia

Lithium can cause hyponatremia by decreasing sodium reabsorption by the renal tubules, leading to sodium depletion. Therefore, it is essential for patients receiving lithium treatment to maintain a normal diet, including salt, and an adequate fluid intake (2500 to 3000 mL) at least during the initial stabilization period. Decreased tolerance to lithium has also been reported to ensue from protracted sweating or diarrhea and, if such occur, supplemental fluid and salt should be administered under careful medical supervision and lithium intake reduced or suspended until the condition is resolved. In addition, concomitant infection with elevated temperatures may also necessitate a temporary reduction or cessation of medication.

Symptoms are also more severe with faster-onset hyponatremia. Mild hyponatremia (i.e., serum Na > 120 mEq/L) can be asymptomatic. Below this threshold, clinical signs are usually present, consisting mainly of changes in mental status, such as altered personality, lethargy, and confusion. For more severe hyponatremia (serum Na < 115 mEq/L), stupor, neuromuscular hyperexcitability, hyperreflexia, seizures, coma, and death can result. During treatment of hyponatremia, serum sodium should not be elevated by more than 10 to 12 mEq/L in 24 hours, or 18 mEq/L in 48 hours. In the case of severe hyponatremia where severe neurologic symptoms are present, a faster infusion rate to correct serum sodium concentration may be needed. Patients rapidly treated or with serum sodium <120mEq/L are more at risk of developing osmotic demyelination syndrome (previously called central pontine myelinolysis). Occurrence is more common among patients with alcoholism, undernutrition, or other chronic debilitating illness. Common signs include flaccid paralysis, dysarthria. In severe cases with extended lesions patients may develop a locked-in syndrome (generalized motor paralysis). Damage often is permanent. If neurologic symptoms start to develop during treatment of hyponatremia, serum sodium correction should be suspended to mitigate the development of permanent neurologic damage.

5.4 Lithium-Induced Chronic Kidney Disease

The predominant form of chronic renal disease associated with long-term lithium treatment is a chronic tubulointerstitial nephropathy (CTIN). The biopsy findings in patients with lithium induced CTIN include tubular atrophy, interstitial fibrosis, sclerotic glomeruli, tubular dilation, and nephron atrophy with cyst formation. The relationship between renal function and morphologic changes and their association with lithium treatment has not been established. CTIN patients might present with nephrotic proteinuria (>3.0g/dL), worsening renal insufficiency and/or nephrogenic diabetes insipidus. Postmarketing cases consistent with nephrotic syndrome in patients with or without CTIN have also been reported. The biopsy findings in patients with nephrotic syndrome include minimal change disease and focal segmental glomerulosclerosis. The discontinuation of lithium in patients with nephrotic syndrome has resulted in remission of nephrotic syndrome.

Kidney function should be assessed prior to and during lithium treatment. Routine urinalysis and other tests may be used to evaluate tubular function (e.g., urine specific gravity or osmolality following a period of water deprivation, or 24-hour urine volume) and glomerular function (e.g., serum creatinine, creatinine clearance, or proteinuria). During lithium treatment, progressive or sudden changes in renal function, even within the normal range, indicate the need for re-evaluation of treatment.

5.5 Encephalopathic Syndrome

An encephalopathic syndrome, characterized by weakness, lethargy, fever, tremulousness and confusion, extrapyramidal symptoms, leukocytosis, elevated serum enzymes, BUN and fasting blood glucose, has occurred in patients treated with lithium and an antipsychotic. In some instances, the syndrome was followed by irreversible brain damage. Because of a possible causal relationship between these events and the concomitant administration of lithium and antipsychotics, patients receiving such combined treatment should be monitored closely for early evidence of neurological toxicity and treatment discontinued promptly if such signs appear. This encephalopathic syndrome may be similar to or the same as neuroleptic malignant syndrome (NMS).

5.6 Serotonin Syndrome

Lithium can precipitate serotonin syndrome, a potentially life-threatening condition. The risk is increased with concomitant use of other serotonergic drugs (including selective serotonin reuptake inhibitors, serotonin and norepinephrine reuptake inhibitors, triptans, tricyclic antidepressants, fentanyl, tramadol, tryptophan, buspirone, and St. John’s Wort) and with drugs that impair metabolism of serotonin, i.e., MAOIs [see Drug Interactions (7.1)].

Serotonin syndrome signs and symptoms may include mental status changes (e.g., agitation, hallucinations, delirium, and coma), autonomic instability (e.g., tachycardia, labile blood pressure, dizziness, diaphoresis, flushing, hyperthermia), neuromuscular symptoms (e.g., tremor, rigidity, myoclonus, hyperreflexia, incoordination), seizures, and gastrointestinal symptoms (e.g., nausea, vomiting, diarrhea).

Monitor all patients taking lithium for the emergence of serotonin syndrome. Discontinue treatment with lithium and any concomitant serotonergic agents immediately if the above symptoms occur, and initiate supportive symptomatic treatment. If concomitant use of lithium with other serotonergic drugs is clinically warranted, inform patients of the increased risk for serotonin syndrome and monitor for symptoms.

5.7 Hypothyroidism or Hyperthyroidism

Lithium is concentrated within the thyroid and can inhibit thyroid synthesis and release which can lead to hypothyroidism. Where hypothyroidism exists, careful monitoring of thyroid function during lithium stabilization and maintenance allows for correction of changing thyroid parameters, if any. Where hypothyroidism occurs during lithium stabilization and maintenance, supplemental thyroid treatment may be used. Paradoxically, some cases of hyperthyroidism have been reported including Grave’s disease, toxic multinodular goiter and silent thyroiditis.

Monitor thyroid function before the initiation of treatment, at three months and every six to twelve months while treatment is ongoing. If serum thyroid tests warrant concern, monitoring should occur more frequently.

5.8 Hypercalcemia and Hyperparathyroidism

Long-term lithium treatment is associated with persistent hyperparathyroidism and hypercalcemia. When clinical manifestations of hypercalcemia are present, lithium withdrawal and change to another mood stabilizer may be necessary. Hypercalcemia may not resolve upon discontinuation of lithium, and may require surgical intervention. Lithium-induced cases of hyperparathyroidism are more often multiglandular compared to standard cases. False hypercalcemia due to plasma volume depletion resulting from nephrogenic diabetes insipidus should be excluded in individuals with mildly increased serum calcium. Monitor serum calcium concentrations regularly.

5.9 Unmasking of Brugada Syndrome

There have been postmarketing reports of a possible association between treatment with lithium and the unmasking of Brugada Syndrome. Brugada Syndrome is a disorder characterized by abnormal electrocardiographic (ECG) findings and a risk of sudden death. Lithium should be avoided in patients with Brugada Syndrome or those suspected of having Brugada Syndrome. Consultation with a cardiologist is recommended if: (1) treatment with lithium is under consideration for patients suspected of having Brugada Syndrome or patients who have risk factors for Brugada Syndrome, e.g., unexplained syncope, a family history of Brugada Syndrome, or a family history of sudden unexplained death before the age of 45 years, (2) patients who develop unexplained syncope or palpitations after starting lithium treatment.

5.10 Pseudotumor Cerebri

Cases of pseudotumor cerebri (increased intracranial pressure and papilledema) have been reported with lithium use. If undetected, this condition may result in enlargement of the blind spot, constriction of visual fields and eventual blindness due to optic atrophy. Consider discontinuing lithium if this syndrome occurs.

6 ADVERSE REACTIONS

The following adverse reactions are described in greater detail in other sections:

- Acute Lithium Toxicity [see Warnings and Precautions (5.1)]
- Lithium-Induced Polyuria [see Warnings and Precautions (5.2)]
- Hyponatremia [see Warnings and Precautions (5.3)]
- Lithium-Induced Chronic Kidney Disease [see Warnings and Precautions (5.4)]
- Encephalopathic Syndrome [see Warnings and Precautions (5.5)]
- Serotonin Syndrome [see Warnings and Precautions (5.6)]
- Hypothyroidism or Hyperthyroidism [see Warnings and Precautions (5.7)]
- Hypercalcemia and Hyperparathyroidism [see Warnings and Precautions (5.8)]
- Unmasking of Brugada Syndrome [see Warnings and Precautions (5.9)]
- Pseudotumor Cerebri [see Warnings and Precautions (5.10)]

6.1 Clinical Trials Experience

Because clinical trials are conducted under widely varying conditions, adverse reaction rates observed in clinical trials of a drug cannot be directly compared to rates in the clinical trials of another drug and may not reflect the rates observed in clinical practice.

Pediatric Patients (7 to 17 years):

Bipolar I Disorder: The following findings are based on an 8-week, placebo-controlled study for acute manic or mixed episodes of bipolar I disorder in pediatric patients 7 to 17 years (N= 81). In this study, lithium was administered at daily doses ranging from 300 to 3600 (mean dose 1483 mg ± 584) with serum levels ranging from 0 to 2.0 (mean level 0.98 mEq/L ± 0.47).

Common Adverse Reactions (incidence ≥ 5% and at least twice the rate of placebo): nausea/vomiting, polyuria, thyroid abnormalities, tremor, thirst/polydipsia, dizziness, rash/dermatitis, ataxia/gait disturbance, decreased appetite, and blurry vision.

Adverse Reactions Occurring at an Incidence of 2% or More in Lithium-Treated Pediatric Patients: Adverse reactions associated with the use of lithium (incidence of 2% or greater, rounded to the nearest percent, and lithium incidence greater than placebo) that occurred during acute therapy (up to 8-weeks in pediatric patients with bipolar disorder) are shown in Table 3.

Table 3: Adverse Reactions Reported in 2% or More of Pediatric Patients on Lithium and That Occurred at Greater Incidence Than in the Placebo Group in the 8-Week Acute Bipolar Trial

System Organ Class/ Preferred Term | Placebo N=28; % | Lithium N=53; %
Gastrointestinal Disorders
1. Nausea/vomiting | 29 | 57
General Disorders
1. Fatigue | 4 | 26
Genitourinary Disorders
1. Polyuria (Including Enuresis) | 14 | 38
Investigations
1. Increased TSH | 0 | 25
Metabolism and nutrition disorders
1. Thirst/polydipsia | 11 | 28
1. Decreased appetite | 4 | 9
Nervous system disorders
1. Ataxia/gait disturbance | 0 | 13
1. Blurry vision | 0 | 9
1. Disorientation | 0 | 6
1. Dizziness | 7 | 23
1. Tremor | 7 | 32
Skin and subcutaneous tissue disorders
1. Rash/dermatitis | 0 | 13

Adult Patients:

The following adverse reactions have been identified following use of lithium. Because these reactions are reported voluntarily from a population of uncertain size, it is not always possible to reliably estimate their frequency or establish a causal relationship to drug exposure.

Central Nervous System: tremor, muscle hyperirritability (fasciculations, twitching, clonic movements of whole limbs), hypertonicity, ataxia, choreoathetotic movements, hyperactive deep tendon reflexes, extrapyramidal symptoms including acute dystonia, cogwheel rigidity, blackout spells, epileptiform seizures, slurred speech, dizziness, vertigo, downbeat nystagmus, incontinence of urine or feces, somnolence, psychomotor retardation, restlessness, confusion, stupor, coma, tongue movements, tics, tinnitus, hallucinations, poor memory, slowed intellectual functioning, startled response, worsening of organic brain syndromes, myasthenic syndromes (rarely).

EEG Changes: diffuse slowing, widening of frequency spectrum, potentiation and disorganization of background rhythm.

Cardiovascular: conduction disturbance (mostly sinus node dysfunction with possibly severe sinus bradycardia and sinoatrial block), ventricular tachyarrhythmia, peripheral vasculopathy (resembling Raynaud’s Syndrome).

ECG Changes: reversible flattening, isoelectricity or rarely inversion of T-waves, prolongation of the QTc interval.

Gastrointestinal: anorexia, nausea, vomiting, diarrhea, gastritis, salivary gland swelling, abdominal pain, excessive salivation, flatulence, indigestion.

Genitourinary: glycosuria, decreased creatinine clearance, albuminuria, oliguria, and symptoms of nephrogenic diabetes insipidus including polyuria, thirst, and polydipsia.

Dermatologic: drying and thinning of hair, alopecia, anesthesia of skin, chronic folliculitis, xerosis cutis, psoriasis onset or exacerbation, generalized pruritus with or without rash, cutaneous ulcers, angioedema, drug reaction with eosinophilia and systemic symptoms (DRESS).

Autonomic Nervous System: blurred vision, dry mouth, impotence/sexual dysfunction.

Miscellaneous: fatigue, lethargy, transient scotoma, exopthalmos, dehydration, weight loss, leukocytosis, headache, transient hyperglycemia, hypermagnesemia, excessive weight gain, edematous swelling of ankles or wrists, dysgeusia/taste distortion (e.g., metallic or salty taste), thirst, swollen lips, tightness in chest, swollen and/or painful joints, fever, polyarthralgia, and dental caries.

7 DRUG INTERACTIONS

7.1 Drugs Having Clinically Important Interactions with Lithium

Table 4: Clinically Important Drug Interactions with Lithium

Diuretics
Clinical Impact: | Diuretic-induced sodium loss may reduce lithium clearance and increase serum lithium concentrations .
Intervention: | More frequent monitoring of serum electrolyte and lithium concentrations. Reduce lithium dosage based on serum lithium concentration and clinical response [see Dosage and Administration (2.3), Warning and Precautions (5.3)].
Non-Steroidal Anti-inflammatory Drugs (NSAID)
Clinical Impact: | NSAID decrease renal blood flow, resulting in decreased renal clearance and increased serum lithium concentrations.
Intervention: | More frequent serum lithium concentration monitoring. Reduce lithium dosage based on serum lithium concentration and clinical response [see Dosage and Administration (2.3)] .
Renin-Angiotensin System Antagonists
Clinical Impact: | Concomitant use increase steady-state serum lithium concentrations.
Intervention: | More frequent monitoring of serum lithium concentration. Reduce lithium dosage based on serum lithium concentration and clinical response [see Dosage and Administration (2.3)] .
Serotonergic Drugs
Clinical Impact: | Concomitant use can precipitate serotonin syndrome.
Intervention: | Monitor patients for signs and symptoms of serotonin syndrome, particularly during lithium initiation. If serotonin syndrome occurs, consider discontinuation of lithium and/or concomitant serotonergic drugs [see Warnings and Precautions (5.6)] .
Nitroimidazole Antibiotics
Clinical Impact: | Concomitant use may increase serum lithium concentrations due to reduced renal clearance.
Intervention: | More frequent monitoring of serum lithium concentration. Reduce lithium dosage based on serum lithium concentration and clinical response [see Dosage and Administration (2.3)] .
Acetazolamide, Urea, Xanthine Preparations, Alkalinizing Agents
Clinical Impact: | Concomitant use can lower serum lithium concentrations by increasing urinary lithium excretion.
Intervention: | More frequent serum lithium concentration monitoring. Increase lithium dosage based on serum lithium concentration and clinical response [see Dosage and Administration (2.3)] .
Methyldopa, Phenytoin and Carbamazepine
Clinical Impact: | Concomitant use may increase risk of adverse reactions of these drugs.
Intervention: | Monitor patients closely for adverse reactions of methyldopa, phenytoin, and carbamazepine.
Iodide Preparations
Clinical Impact: | Concomitant use may produce hypothyroidism.
Intervention: | Monitor patients for signs or symptoms of hypothyroidism [see Warnings and Precautions (5.7)] .
Calcium Channel Blocking Agents (CCB)
Clinical Impact: | Concomitant use may increase the risk of neurologic adverse reactions in the form of ataxia, tremors, nausea, vomiting, diarrhea and/or tinnitus.
Intervention: | Monitor for neurologic adverse reactions.
Atypical and Typical Antipsychotic Drugs
Clinical Impact: | Reports of neurotoxic reactions in patients treated with both lithium and an antipsychotic, ranging from extrapyramidal symptoms to neuroleptic malignant syndrome, as well as reports of an encephalopathic syndrome in few patients treated with concomitant therapy [see Warnings and Precautions (5.5)] .
Intervention: | Monitor for neurologic adverse reactions.
Sodium-Glucose Cotransporter 2 (SGLT2) inhibitor
Clinical Impact: | Concomitant use of lithium with an SGLT2 inhibitor may decrease serum lithium concentrations.
Intervention: | Monitor serum lithium concentration more frequently during SGLT2 inhibitor initiation and dosage changes.
Neuromuscular Blocking Agents
Clinical Impact: | Lithium may prolong the effects of neuromuscular blocking agents.
Intervention: | Monitor for prolonged paralysis.

8 USE IN SPECIFIC POPULATIONS

8.1 Pregnancy

Risk Summary:

Lithium may cause harm when administered to a pregnant woman. Early voluntary reports to international birth registries suggested an increase in cardiovascular malformations, especially for Ebstein’s anomaly, with first trimester use of lithium. Subsequent case-control and cohort studies indicate that the increased risk for cardiac malformations is likely to be small; however, the data are insufficient to establish a drug-associated risk. There are concerns for maternal and/or neonatal lithium toxicity during late pregnancy and the postpartum period [see Clinical Considerations]. Published animal developmental and toxicity studies in mice and rats report an increased incidence of fetal mortality, decreased fetal weight, increased fetal skeletal abnormalities, and cleft palate (mouse fetuses only) with oral doses of lithium that produced serum concentrations similar to the human therapeutic range. Other published animal studies report adverse effects on embryonic implantation in rats after lithium administration. Advise pregnant women of the potential risk to a fetus.

The background risk of major birth defects and miscarriage for the indicated population(s) is unknown. In the U.S. general population, the estimated background risk of major birth defects and miscarriage in clinically recognized pregnancies is 2 to 4% and 15 to 20%, respectively.

Clinical Considerations:

Dose Adjustments During Pregnancy and the Postpartum Period: If the decision is made to continue lithium treatment during pregnancy, serum lithium concentrations should be monitored and the dosage adjusted during pregnancy. Two to three days prior to delivery, lithium dosage should be decreased or discontinued to reduce the risk of maternal and/or neonatal toxicity. Lithium may be restarted in the post-partum period at preconception doses in medically stable patients as long as serum lithium levels are closely monitored [see Dosage and Administration (2.4), Warnings and Precautions (5.1)] .

Fetal/Neonatal Adverse Reactions: Lithium toxicity may occur in neonates who were exposed to lithium in late pregnancy. A floppy baby syndrome including neurological, cardiac, and hepatic abnormalities that are similar to those seen with lithium toxicity in adults have been observed. Symptoms include hypotonia, respiratory distress syndrome, cyanosis, lethargy, feeding difficulties, depressed neonatal reflexes, neonatal depression, apnea, and bradycardia. Monitor neonates and provide supportive care until lithium is excreted and toxic signs disappear, which may take up to 14 days.

Consider fetal echocardiography between 16 and 20 weeks gestation in a woman with first trimester lithium exposure because of the potential increased risk of cardiac malformations.

8.2 Lactation

Risk Summary:

Limited published data reports the presence of lithium carbonate in human milk with breast milk levels measured at 0.12 to 0.7 mEq or 40 to 45% of maternal plasma levels. Infants exposed to lithium during breastfeeding may have plasma levels that are 30 to 40% of maternal plasma levels. Signs and symptoms of lithium toxicity such as hypertonia, hypothermia, cyanosis, and ECG changes have been reported in some breastfed neonates and infants. Increased prolactin levels have been measured in lactating women, but the effects on milk production are not known. Breastfeeding is not recommended with maternal lithium use; however, if a woman chooses to breastfeed, the infant should be closely monitored for signs of lithium toxicity. Discontinue breastfeeding if a breastfed infant develops lithium toxicity.

Clinical Considerations:

Consider regular monitoring of lithium levels and thyroid function in a breastfed infant.

8.4 Pediatric Use

The safety and effectiveness of lithium for monotherapy treatment of acute manic or mixed episodes of bipolar I disorder and maintenance monotherapy of bipolar I disorder in pediatric patients ages 7 to 17 years of age have been established in an acute-phase clinical trial of 8 weeks in duration followed by a 28-week randomized withdrawal phase [see Dosage and Administration (2.1), Adverse Reactions (6.1), Clinical Pharmacology (12.3), Clinical Studies (14)] .

The safety and effectiveness of lithium has not been established in pediatric patients less than 7 years of age with bipolar I disorder.

8.5 Geriatric Use

Clinical studies of lithium carbonate tablets did not include sufficient numbers of subjects aged 65 and over to determine whether they respond differently from younger subjects. Other reported clinical experience has not identified differences in response between the elderly and younger patients. In general, dose selection for an elderly patient should be cautious, usually starting at the low end of the dosing range, reflecting the greater frequency of decreased hepatic, renal, or cardiac function, and of concomitant disease or other treatment.

Lithium is known to be substantially excreted by the kidneys, and the risk of toxic reactions to this drug may be greater in patients with impaired renal function. Because elderly patients are more likely to have decreased renal function, care should be taken in dose selection, and it may be useful to monitor renal function.

8.6 Renal Impairment

As lithium is eliminated primarily through the kidney, lithium renal clearance is decreased in patients with abnormal renal function, and the risk of lithium intoxication increases considerably in this setting. Lithium should not be used in severe renal insufficiency (creatinine clearance less than 30 mL/min evaluated by Cockcroft-Gault), especially if the condition requires adherence to a low-sodium diet [see Dosage and Administration (2.5)] .

Start patients with mild to moderately impaired renal function (creatinine clearance 30 to 89 mL/min evaluated by Cockcroft-Gault) with lower doses of lithium and titrate slowly while frequently monitoring serum lithium concentrations and for signs of lithium toxicity [see Dosage and Administration (2.5)].

10 OVERDOSAGE

The toxic concentrations for lithium (≥ 1.5 mEq/L) are close to the therapeutic concentrations [see Warnings and Precautions (5.1)] . At lithium concentrations greater than 3 mEq/L, patients may progress to seizures, coma, and irreversible brain damage.

Treatment:

For current information on the management of poisoning or overdosage, contact the National Poison Control Center at 1-800-222-1222 or www.poison.org.

No specific antidote for lithium poisoning is known. Mild symptoms of lithium toxicity can usually be treated by reduction in dose or cessation of the drug.

In severe cases of lithium poisoning, the goal of treatment is elimination of this ion from the patient. Administration of gastric lavage should be performed, but use of activated charcoal is not recommended as it does not significantly absorb lithium ions. Hemodialysis is the treatment of choice as it is an effective and rapid means of removing lithium in patients with severe toxicity. As an alternative option, urea, mannitol and aminophylline can induce a significant increase in lithium excretion. Appropriate supportive care for the patient should be undertaken. Patients with impaired consciousness should have their airway protected and it is critical to correct any volume depletion or electrolyte imbalance. Patients should be monitored to prevent hypernatremia while receiving normal saline and careful regulation of kidney function is of utmost importance.

Serum lithium concentrations should be closely monitored as there may be a rebound in serum lithium concentrations as a result of delayed diffusion from the body tissues. Likewise, during the late recovery phase, lithium should be re-administered with caution taking into account the possible release of significant lithium stores in body tissues.

11 DESCRIPTION

Each tablet for oral administration contains lithium carbonate USP, 300 mg and the following inactive ingredients: calcium stearate, microcrystalline cellulose, povidone, purified water, sodium lauryl sulfate, and sodium starch glycolate.

Each capsule for oral administration contains lithium carbonate USP, 150 mg, 300 mg or 600 mg and the following inactive ingredient: talc. The capsule shells contain black monogramming ink, FD&C Red No. 40 (300 mg and 600 mg only), gelatin and titanium dioxide. The black monogramming ink contains ammonium hydroxide, ethanol, iron oxide black, isopropyl alcohol, N-butyl alcohol, propylene glycol and shellac glaze.

Each 5 mL of solution for oral administration contains lithium ion (Li+), 8 mEq (equivalent to amount of lithium in 300 mg of lithium carbonate), alcohol 0.3% v/v and the following other inactive ingredients: citric acid, purified water, raspberry blend, sodium benzoate and sorbitol solution.

Lithium Oral Solution is a palatable oral dosage form of lithium ion. It is prepared in solution from lithium hydroxide and citric acid in a ratio approximately di-lithium citrate.

Lithium is an element of the alkali-metal group with atomic number 3, atomic weight 6.94, and an emission line at 671 nm on the flame photometer.

The empirical formula for Lithium Citrate is C6H5Li3O7; molecular weight 209.93. Lithium acts as an antimanic.

Lithium Carbonate USP is a granular, white powder with molecular formula Li2CO3 and molecular weight 73.89.

12 CLINICAL PHARMACOLOGY

12.1 Mechanism of Action

The mechanism of action of lithium as a mood stabilizing agent is unknown.

12.3 Pharmacokinetics

Absorption:

After oral administration, lithium is reported to be completely absorbed in the upper gastrointestinal tract. Peak serum concentrations (Tmax) occur 0.25 to 3 hours after oral administration of immediate release preparations and 2 to 6 hours after sustained-release preparations.

Distribution:

The distribution space of lithium approximates that of total body water, and the plasma protein binding is negligible. After equilibrium, the apparent volume of distribution is 0.7 to 1 L/kg.

Metabolism:

Lithium is not metabolized.

Excretion:

Lithium is primarily excreted in urine, proportionally to its serum concentration. Lithium is filtered by the glomerulus, and 80% is reabsorbed by passive diffusion in the proximal tubule. The elimination half-life of lithium is approximately 18 to 36 hours. Lithium excretion in feces is insignificant.

Specific Populations:

Pediatric Use: A pharmacokinetic study of lithium was performed in 39 subjects with bipolar I disorder. Both apparent clearance and apparent volume of distribution increase as body weight increases. A lower dose in patients < 30 kg is necessary to achieve lithium exposures in pediatric patients similar to those observed in adults treated at recommended doses of lithium [see Dosage and Administration (2.2)] . The estimated plasma clearance was 0.59 L/h, 0.79 L/h and 1.17 L/h for pediatric patients weighing 20 kg, 30 kg and 50 kg, respectively.

13 NONCLINICAL TOXICOLOGY

13.1 Carcinogenesis, Mutagenesis, Impairment of Fertility

Carcinogenesis:

There have been no long-term studies performed in animals to evaluate the carcinogenic potential of lithium.

Mutagenesis:

There have been no adequate studies conducted to evaluate the mutagenic and genotoxic potential of lithium.

Impairment of Fertility:

There have been no adequate studies performed in animals at current standards to evaluate the effect of lithium treatment on fertility. However, published studies in male mice and rats administered repeated daily dosing of lithium carbonate report adverse effects on male reproductive organs, decreased spermatogenesis and decreased testosterone levels.

14 CLINICAL STUDIES

The safety and efficacy of lithium as a treatment for acute manic or mixed episodes of bipolar I disorder in pediatric patients (ages 7 to ≤18 years) was demonstrated in an 8-week, randomized, placebo-controlled, parallel group study (NCT01166425). In this study, 81 patients with a Young Mania Rating Scale (YMRS) score of 20 or more were randomized to receive lithium or placebo in a 2:1 ratio. Patients weighing more than 30 kg started lithium at 300 mg three times daily (900 mg/day) and could increase their dose by 300 mg every 3 days. Patients weighing 20 to 30 kg started lithium at 300 mg twice daily (600 mg/day) and could increase their dose by 300 mg weekly. No patients weighing less than 20 kg were enrolled. Lithium (mean serum level 0.98 ± 0.47 mEq/L) was statistically significantly superior to placebo in decreasing acute mania or mixed states as measured by the YMRS (see Table 5).

In a 28-week randomized withdrawal analysis, 31 pediatric patients stabilized on lithium were assigned to either continue lithium or switch to placebo. The group receiving lithium demonstrated superiority to those receiving placebo in all-cause discontinuation (see Table 5).

Table 5: Primary Efficacy Results

Analysis | Treatment Group | Change From Baseline at Week 8 in YMRS Summary Score
Analysis | Treatment Group | N | Mean Baseline Score (SD) | LS Mean Change from Baseline (SE) | Difference [Difference (drug minus placebo) in least-squares mean change from baseline.] (95% CI)
Acute Efficacy | Lithium: | 53 | 29.5 (5.6) | -12.9 (3.1) | -5.5 (-10.5, -0.5)
Acute Efficacy | Placebo: | 28 | 30.0 (6.0) | -7.3 (3.1) | -5.5 (-10.5, -0.5)
Analysis | Treatment Group [Patients analyzed by received treatment.] | All-cause Discontinuation
Analysis | Treatment Group [Patients analyzed by received treatment.] | N |  | Number of Discontinued Subjects | Hazard Ratio [Lithium to placebo.]; (95% CI)
Randomized Withdrawal | Lithium: | 17 |  | 7 (41.2%) | 0.28 (0.10, 0.78)
Randomized Withdrawal | Placebo: | 14 |  | 11 (78.6%) | 0.28 (0.10, 0.78)
SD: standard deviation; SE: standard error; LS Mean: least-squares mean; CI: confidence interval.

16 HOW SUPPLIED/STORAGE AND HANDLING

Lithium Carbonate Tablets USP

300 mg supplied as white to off-white, biconvex tablet, scored on one side with product identification “54 452” debossed on the other side.

NDC: 70518-1481-00

NDC: 70518-1481-01

PACKAGING: 30 in 1 BLISTER PACK

PACKAGING: 30 in 1 BLISTER PACK

Storage

Store at 20°C to 25°C (68°F to 77°F); excursions permitted to 15°C to 30°C (59°F to 86°F). [See USP Controlled Room Temperature.] Dispense in a tight, child-resistant container as defined in the USP/NF. PROTECT FROM MOISTURE.

Repackaged and Distributed By:

Remedy Repack, Inc.

625 Kolter Dr. Suite #4 Indiana, PA 1-724-465-8762

17 PATIENT COUNSELING INFORMATION

Advise the patient to read FDA-approved patient labeling (Medication Guide).

Dosage and Administration:

Advise patients that lithium is a mood stabilizer, and should only be taken as directed. Emphasize the importance of compliance with the prescribed treatment and to not adjust the dose of lithium without first consulting their healthcare provider. Inform patients that they will need to have regular blood draws to determine if their dose of lithium is appropriate.

Instruct patients not to double the dose if a dose is missed, due to the complexity of individualized dosing and potential for lithium toxicity [see Dosage and Administration (2), Warnings and Precautions (5.1)] .

Lithium Toxicity:

Inform patients on adverse reactions related to lithium toxicity that require medical attention. Advise patients to discontinue lithium treatment and contact their healthcare provider if clinical signs of lithium toxicity such as diarrhea, vomiting, tremor, lack of muscle coordination, drowsiness, abnormal heart rhythm or muscular weakness occur [see Warnings and Precautions (5.1)] .

Lithium-Induced Polyuria:

Counsel patients on the adverse reactions related to lithium-induced polyuria, when to seek medical attention, and the importance of maintaining normal diet with salt and staying hydrated [see Warnings and Precautions (5.2)] .

Hyponatremia:

Counsel patients on the adverse reactions of hyponatremia, when to seek medical attention, the importance of maintaining a normal diet including adequate salt intake and staying hydrated [see Warnings and Precautions (5.3)] . Salt supplements and additional fluids may be required if excessive losses occur.

Serotonin Syndrome:

Caution patients about the risk of serotonin syndrome, particularly with the concomitant use of lithium with other serotonergic drugs including SSRIs, SNRIs, triptans, tricyclic antidepressants, fentanyl, tramadol, tryptophan, buspirone, St. John’s Wort, and with drugs that impair metabolism of serotonin (in particular, MAOIs, both those intended to treat psychiatric disorders and also others, such as linezolid) [see Warnings and Precautions (5.6) and Drug Interactions (7)] .

Drug Interactions:

Advise patients that many drugs can interact with lithium and to inform their doctor and pharmacist if they are taking any over the counter medication, including herbal medication, or are started on a new prescription [see Drug Interactions (7)] .

Somnolence:

Tell patients that lithium may cause somnolence particularly when initiating treatment and to be cautious about operating vehicles or hazardous machinery, until they are reasonably certain that lithium treatment does not affect them adversely [see Adverse Reactions (6)].

Pregnancy:

Advise pregnant women of the potential risk to a fetus and/or neonate [see Use in Specific Populations (8.1)] .

Lactation:

Advise women that breastfeeding is not recommended during treatment with lithium [see Use in Specific Populations (8.2)] .

Repackaged By / Distributed By: RemedyRepack Inc.

625 Kolter Drive, Indiana, PA 15701

(724) 465-8762

Medication Guide

Lithium (LITH-ee-əm) oral solution

Lithium Carbonate tablets

Lithium Carbonate capsules

What is the most important information I should know about Lithium and Lithium Carbonate?

Lithium and Lithium Carbonate can cause serious side effects, including:

- too much lithium in your blood (lithium toxicity). Lithium toxicity that can cause death may happen even if the lithium level in your blood is close to the right level for you. Your healthcare provider will need to monitor your blood levels of lithium to find the best dose for you. Take your Lithium or Lithium Carbonate exactly as your healthcare provider tells you to take it. Stop taking Lithium and Lithium Carbonate and call your healthcare provider right away if you have any symptoms of lithium toxicity including:

- abnormal heartbeat

- vomiting

- diarrhea

- drowsiness

- weak muscles

- blurred vision

- clumsiness

- ringing in your ears

- muscle twitching

Other symptoms may include:

- lightheadedness

- confusion

- bloating

- mood changes

- slurred speech

- breathing problems

- seizure

- coma

What is Lithium and Lithium Carbonate?

Lithium and Lithium Carbonate are prescription medicines called mood-stabilizing agents used alone (monotherapy) for:

- the acute (short-term) treatment of people 7 years of age and older with manic and mixed episodes that happen with bipolar I disorder.
- maintenance treatment of bipolar I disorder in people 7 years of age and older.

It is not known if Lithium and Lithium Carbonate are safe and effective in children under 7 years of age with bipolar I disorder.

Who should not take Lithium or Lithium Carbonate?

Do not take Lithium or Lithium Carbonate if you are allergic to Lithium or any of the ingredients in Lithium Carbonate or Lithium Citrate. See the end of this Medication Guide for a complete list of ingredients in Lithium and Lithium Carbonate.

What should I tell my healthcare provider before taking Lithium or Lithium Carbonate?

Before taking Lithium or Lithium Carbonate, tell your healthcare provider if you:

- have kidney problems

- have heart problems

- have breathing problems

- have thyroid problems

- are pregnant or plan to become pregnant. Lithium and Lithium Carbonate may harm your
  unborn baby.

- are breastfeeding or plan to breastfeed. Lithium and Lithium Carbonate can pass into your breastmilk and may harm your baby. You should not breastfeed during treatment with Lithium or Lithium Carbonate. Talk to your healthcare provider about the best way to feed your baby if you take Lithium or Lithium Carbonate.

Tell your healthcare provider about all the medicines you take, including prescription, over-the-counter medicines, vitamins, and herbal supplements.

Using Lithium and Lithium Carbonate with certain other medicines may affect each other causing possible side effects. Lithium and Lithium Carbonate may affect the way other medicines work, and other medicines may affect how Lithium and Lithium Carbonate works.

Especially tell your healthcare provider if you take:

- MAOIs

- selective serotonin reuptake inhibitors (SSRIs)

- serotonin norepinephrine reuptake inhibitors (SNRIs)

- medicines used to treat migraine headaches called triptans

- tricyclic antidepressants

- fentanyl

- antipsychotic medicines

- tramadol

- tryptophan

- buspirone

- St. John’s Wort

Your healthcare provider can tell you if it is safe to take Lithium or Lithium Carbonate with your other medicines. Do not start or stop any medicines while taking Lithium or Lithium Carbonate without talking to your healthcare provider first.

Know the medicines you take. Keep a list of your medicines to show your healthcare provider and pharmacist when you get a new medicine.

How should I take Lithium and Lithium Carbonate?

- Take your Lithium and Lithium Carbonate exactly as prescribed by your healthcare provider.

- Your healthcare provider will do certain blood tests before starting and during treatment with Lithium and Lithium Carbonate.

- Your healthcare provider may change your dose if needed. Do not change your dose on your own.

- Do not double your dose if a dose is missed. Talk with your healthcare provider if you miss a dose.

- Do not stop taking Lithium or Lithium Carbonate suddenly without talking to your healthcare provider.

- Your healthcare provider may change your Lithium or Lithium Carbonate dose to make sure you are taking the dose that is right for you.

- If you take too much Lithium or Lithium Carbonate, call your healthcare provider or poison control center, or go to the nearest hospital emergency room right away. In case of poisoning, call your poison control center at 1-800-222-1222.

What should I avoid while taking Lithium or Lithium Carbonate?

- Do not drive, operate heavy machinery, or do other dangerous activities when you start taking Lithium or Lithium Carbonate, when your dose is changed, or until you know how Lithium or Lithium Carbonate affects you. Lithium or Lithium Carbonate can make you sleepy. Talk to your healthcare provider about these activities.

- Avoid becoming overheated or dehydrated during exercise and in hot weather. Follow your healthcare provider instructions about the type and amount of liquids you should drink. In some cases, drinking too much liquid can be as unsafe as not drinking enough.

- Do not change the amount of salt in your diet. Changing the amount of salt in your diet could change the amount of Lithium or Lithium Carbonate in your blood.

What are the possible side effects of Lithium and Lithium Carbonate?

See “What is the most important information I should know about Lithium and Lithium Carbonate?”

Lithium and Lithium Carbonate may cause serious side effects, including:

- kidney problems. People who take Lithium or Lithium Carbonate may have to urinate often (polyuria) and have other kidney problems that may affect how their kidneys work. These problems can happen within a few weeks of starting to take Lithium or Lithium Carbonate or after taking Lithium or Lithium Carbonate for a long time.

- low levels of sodium (salt) in your blood (hyponatremia). Lithium and Lithium Carbonate can cause you to lose sodium. Talk to your healthcare provider about your diet and how much fluid you are drinking when starting Lithium or Lithium Carbonate. If you have been sweating more than usual or have had diarrhea, you may need extra salt and more fluids. Talk to your healthcare provider if this happens.

- neurological problems. People who take Lithium or Lithium Carbonate with certain other medicines called antipsychotics may have symptoms such as weakness, tiredness, fever, tremors, and confusion. Talk to your healthcare provider if this happens. Ask if you are not sure about the medicines you take.

- serotonin syndrome. A potentially life-threatening problem called serotonin syndrome can happen when you take Lithium or Lithium Carbonate while you take certain medicines called serotonergic and MAOIs. Symptoms of serotonin syndrome include:

- agitation

- seeing things that are not there

- confusion

- coma

- rapid pulse

- high or low blood pressure

- dizziness

- sweating

- flushing

- fever

- tremors

- stiff muscles

- muscle twitching

- become unstable

- seizures

- nausea

- vomiting

- diarrhea

- thyroid problems.

- high calcium levels in your blood (hypercalcemia) and changes in your parathyroid gland (hyperparathyroidism) that may not go away when you stop taking Lithium or Lithium Carbonate.

- heart problems. People who take Lithium or Lithium Carbonate may find out they also have a heart problem called Brugada Syndrome. People who have unexplained fainting or who have a family history of sudden unexplained death before 45 years of age may have Brugada Syndrome and not know it. If you faint or feel abnormal heartbeats, talk to your healthcare provider right away.

- increased pressure in the brain and swelling in the eye (pseudotumor cerebri) that can cause vision problems or blindness. If you have severe headaches behind your eyes, ringing in the ears, blurred vision, double vision, or brief periods of blindness, talk to your health care provider right away.

The most common side effects of Lithium and Lithium Carbonate, include:

- Adults with manic or mixed episodes of bipolar I disorder:

- hand trembling

- excessive urination

- increased thirst

- nausea

- general discomfort when you start treatment

- Children 7 to 17 years of age with manic or mixed episodes of bipolar I disorder:

- excessive urination

- thyroid problems

- hand trembling

- excessive thirst

- dizziness

- rash

- difficulty walking

- decreased appetite

- blurred vision

- nausea

- vomiting

These are not all the possible side effects of Lithium and Lithium Carbonate.

Call your doctor for medical advice about side effects. You may report side effects to FDA at 1-800-FDA-1088.

How should I store Lithium and Lithium Carbonate?

Store Lithium and Lithium Carbonate at room temperature, between 68°F to 77°F (20°C to 25°C).

Keep capsules and tablets dry and keep in a tightly closed container.

Keep Lithium, Lithium Carbonate, and all medicines out of the reach of children.

General information about the safe and effective use of Lithium and Lithium Carbonate.

Medicines are sometimes prescribed for purposes other than those listed in a Medication Guide. Do not use Lithium or Lithium Carbonate for a condition for which it was not prescribed. Do not give Lithium or Lithium Carbonate to other people, even if they have the same symptoms you have. It may harm them. You can ask your pharmacist or healthcare provider for information about Lithium or Lithium Carbonate that is written for healthcare professionals.

For more information about Lithium and Lithium Carbonate, please call West-Ward Pharmaceuticals Corp. at 1-800-962-8364.

What are the ingredients in Lithium and Lithium Carbonate?

Active ingredient: lithium carbonate, USP (tablets and capsules) and lithium citrate (oral solution).

Inactive ingredients:

Tablets: calcium stearate, microcrystalline cellulose, povidone, purified water, sodium lauryl sulfate, and sodium starch glycolate.

Capsules: talc. The capsule shells contain black monogramming ink, FD&C Red No. 40 (300 mg and 600 mg only), gelatin and titanium dioxide. The black monogramming ink contains ammonium hydroxide, ethanol, iron oxide black, isopropyl alcohol, N-butyl alcohol, propylene glycol and shellac glaze.

Oral solution: alcohol 0.3%, citric acid, purified water, raspberry blend, sodium benzoate and sorbitol solution.

This Medication Guide has been approved by the U.S. Food and Drug Administration.

Revised 10 2020

10008909/10

Repackaged By / Distributed By: RemedyRepack Inc.

625 Kolter Drive, Indiana, PA 15701

(724) 465-8762

PRINCIPAL DISPLAY PANEL

DRUG: Lithium Carbonate

GENERIC: Lithium Carbonate

DOSAGE: TABLET

ADMINSTRATION: ORAL

NDC: 70518-1481-0

NDC: 70518-1481-1

COLOR: white

SHAPE: ROUND

SCORE: Two even pieces

SIZE: 10 mm

IMPRINT: 54;452

PACKAGING: 30 in 1 BLISTER PACK

PACKAGING: 30 in 1 BLISTER PACK

ACTIVE INGREDIENT(S):

- LITHIUM CARBONATE 300mg in 1

INACTIVE INGREDIENT(S):

- CALCIUM STEARATE
- MICROCRYSTALLINE CELLULOSE
- POVIDONE K30
- SODIUM LAURYL SULFATE
- SODIUM STARCH GLYCOLATE TYPE A POTATO
- WATER